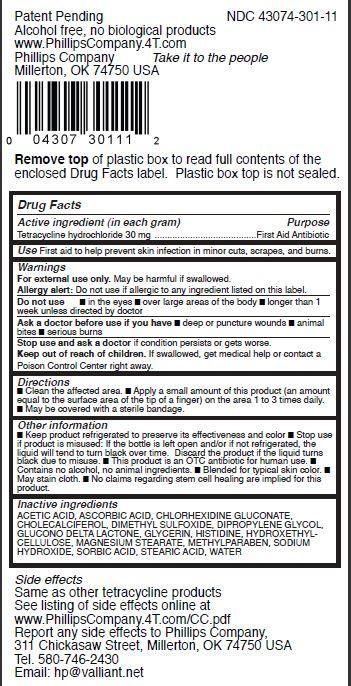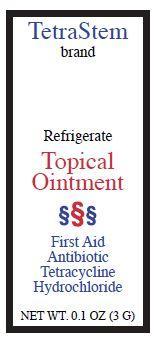 DRUG LABEL: TetraStem
NDC: 43074-301 | Form: OINTMENT
Manufacturer: Phillips Company
Category: otc | Type: HUMAN OTC DRUG LABEL
Date: 20140225

ACTIVE INGREDIENTS: TETRACYCLINE HYDROCHLORIDE 30 mg/1 g
INACTIVE INGREDIENTS: ACETIC ACID; ASCORBIC ACID; CHLORHEXIDINE GLUCONATE; CHOLECALCIFEROL; DIMETHYL SULFOXIDE; DIPROPYLENE GLYCOL; GLUCONOLACTONE; GLYCERIN; HISTIDINE; MAGNESIUM STEARATE; METHYLPARABEN; SODIUM HYDROXIDE; SORBIC ACID; STEARIC ACID; WATER

TetraStem - Topical Ointment

Active ingredient (in each gram)

Tetracycline hydrochloride 30 mg

Purpose

First Aid Antibiotic

Use

First aid to help prevent skin infection in minor cuts, scrapes, and burns.

Warnings

For external use only. May be harmful if swallowed.
Allergy alert: Do not use if allergic to any ingredient listed on this label.

Do not use

- in the eyes
- over large areas of the body
- longer than 1 week unless directed by doctor

Ask a doctor before use if you have

- deep or puncture wounds
- animal bites
- serious burns

Stop use and ask a doctor

if condition persists or gets worse.

Keep out of reach of children.

If swallowed, get medical help or contact a Poison Control Center right away.

Directions

- Clean the affected area.
- Apply a small amount of this product (an amount equal to the surface area of the tip of a finger) on the area 1 to 3 times daily.
- May be covered with a sterile bandage.

Other information

- Keep product refrigerated to preserve its effectiveness and color
- Stop use if product is misused: If the bottle is left open and/or if not refrigerated, the liquid will tend to turn black over time. Discard the product if the liquid turns black due to misuse.
- This product is an OTC antibiotic for human use.
- Contains no alcohol, no animal ingredients.
- Blended for typical skin color.
- May stain cloth.
- No claims regarding stem cell healing are implied for this product.

Inactive ingredients

ACETIC ACID, ASCORBIC ACID, CHLORHEXIDINE GLUCONATE,
CHOLECALCIFEROL, DIMETHYL SULFOXIDE, DIPROPYLENE GLYCOL,
GLUCONO DELTA LACTONE, GLYCERIN, HISTIDINE, HYDROXETHYLCELLULOSE,
MAGNESIUM STEARATE, METHYLPARABEN, SODIUM
HYDROXIDE, SORBIC ACID, STEARIC ACID, WATER

Package Label

TetraStem
brand

Refrigerate
Topical
Ointment

First Aid
Antibiotic
Tetracycline
Hydrochloride

NET WT. 0.1 OZ (3 G)

Patent Pending NDC 43074-301-11
Alcohol free, no biological products
www.PhillipsCompany.4T.com
Phillips Company Take it to the people
Millerton, OK 74750 USA

Remove top of plastic box to read full contents of the
enclosed Drug Facts label. Plastic box top is not sealed.

Side effects
Same as other tetracycline products
See listing of side effects online at
www.PhillipsCompany.4T.com/CC.pdf
Report any side effects to Phillips Company,
311 Chickasaw Street, Millerton, OK 74750 USA
Tel. 580-746-2430
Email: hp@valliant.net TetraStem